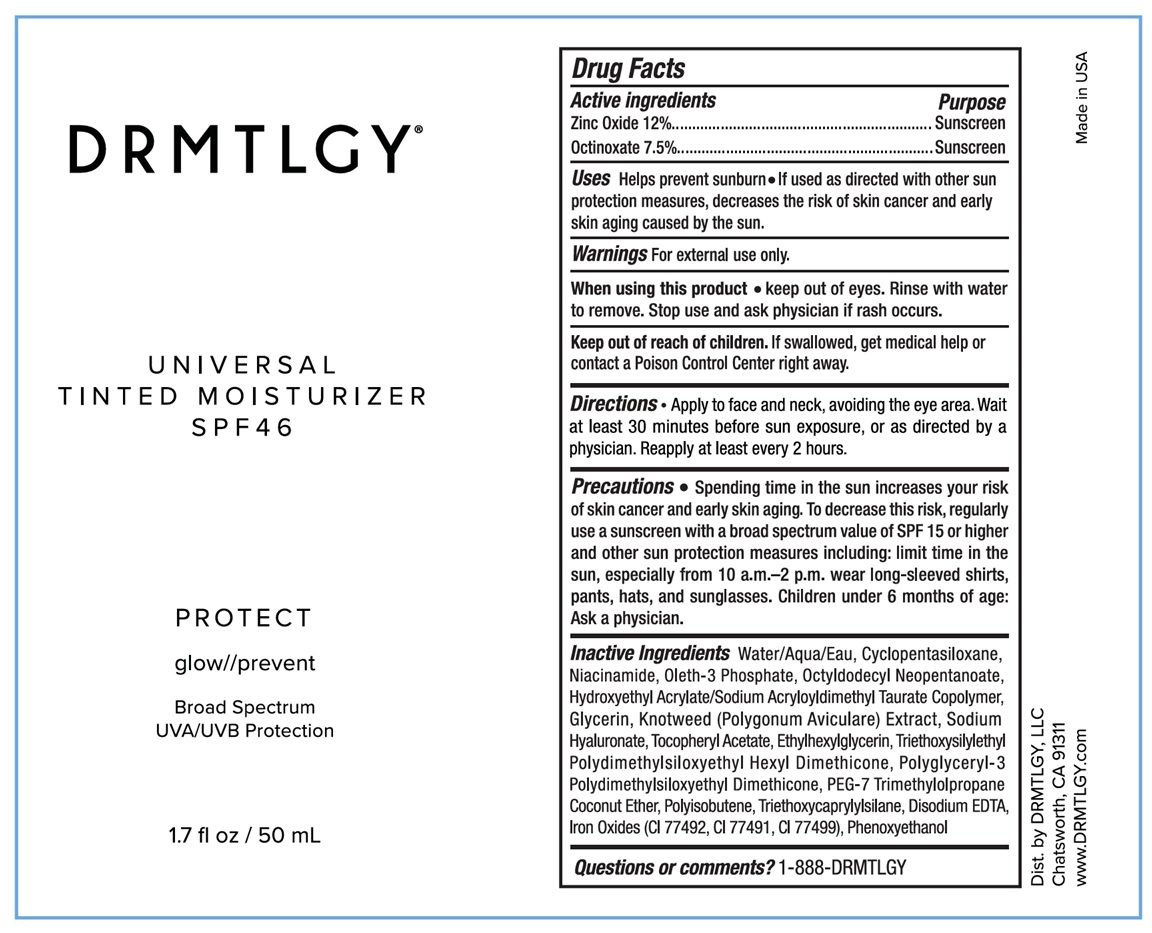 DRUG LABEL: Tinted Moisturizer SPF 46 Universal Tint
NDC: 83286-009 | Form: CREAM
Manufacturer: Drmtlgy, LLC
Category: otc | Type: HUMAN OTC DRUG LABEL
Date: 20251111

ACTIVE INGREDIENTS: ZINC OXIDE 12 g/100 mL; OCTINOXATE 7.5 g/100 mL
INACTIVE INGREDIENTS: WATER; CYCLOMETHICONE 5; NIACINAMIDE; OLETH-3 PHOSPHATE; OCTYLDODECYL NEOPENTANOATE; HYDROXYETHYL ACRYLATE/SODIUM ACRYLOYLDIMETHYL TAURATE COPOLYMER (100000 MPA.S AT 1.5%); GLYCERIN; POLYGONUM AVICULARE TOP; HYALURONATE SODIUM; .ALPHA.-TOCOPHEROL ACETATE; ETHYLHEXYLGLYCERIN; TRIETHOXYSILYLETHYL POLYDIMETHYLSILOXYETHYL HEXYL DIMETHICONE; POLYGLYCERYL-3 POLYDIMETHYLSILOXYETHYL DIMETHICONE (4000 MPA.S); PEG-7 TRIMETHYLOLPROPANE COCONUT ETHER; POLYISOBUTYLENE (1000 MW); TRIETHOXYCAPRYLYLSILANE; EDETATE DISODIUM; FERRIC OXIDE YELLOW; FERRIC OXIDE RED; FERROSOFERRIC OXIDE; PHENOXYETHANOL

DRMTLGY® Tinted Moisturizer SPF 46 Universal Tint

Active ingredients

Zinc Oxide 12%

Octinoxate 7.5%

Purpose

Sunscreen

Uses

Helps prevent sunburn • If used as directed with other sun protection measures, decreases the risk of skin cancer and early skin aging caused by the sun.

Warnings

For external use only.

When using this product • keep out of eyes. Rinse with water to remove. Stop use and ask physician if rash occurs.

Keep out of reach of children. If swallowed, get medical help or contact a Poison Control Center right away.

Directions

• Apply to face and neck, avoiding the eye area. Wait at least 30 minutes before sun exposure, or as directed by a physician. Reapply at least every 2 hours.

Precautions

• Spending time in the sun increases your risk of skin cancer and early skin aging. To decrease this risk, regularly use a sunscreen with a broad spectrum value of SPF 15 or higher and other sun protection measures including: limit time in the sun, especially from 10 a.m.-2 p.m. wear long-sleeved shirts, pants, hats, and sunglasses. Children under 6 months of age: Ask a physician.

Inactive Ingredients

Water/Aqua/Eau, Cyclopentasiloxane, Niacinamide, Oleth-3 Phosphate, Octyldodecyl Neopentanoate, Hydroxyethyl Acrylate/Sodium Acryloyldimethyl Taurate Copolymer, Glycerin, Knotweed (Polygonum Aviculare) Extract, Sodium Hyaluronate, Tocopheryl Acetate, Ethylhexylglycerin, Triethoxysilylethyl Polydimethylsiloxyethyl Hexyl Dimethicone, Polyglyceryl-3 Polydimethylsiloxyethyl Dimethicone, PEG-7 Trimethylolpropane Coconut Ether, Polyisobutene, Triethoxycaprylylsilane, Disodium EDTA, Iron Oxides (CI 77492, CI 77491, CI 77499), Phenoxyethanol

Questions or comments?

1-888-DRMTLGY

PROTECT

glow//prevent

Broad Spectrum
UVA/UVB Protection

Dist. by DRMTLGY, LLC
Chatsworth, CA 91311
www.DRMTLGY.com

Made in USA